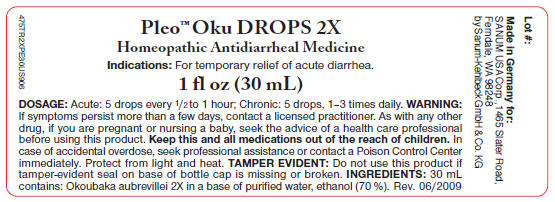 DRUG LABEL: Pleo Oku
NDC: 60681-2401 | Form: SOLUTION/ DROPS
Manufacturer: Sanum Kehlbeck GmbH & Co. KG
Category: homeopathic | Type: HUMAN OTC DRUG LABEL
Date: 20091130

ACTIVE INGREDIENTS: OKOUBAKA AUBREVILLEI BARK 2 [hp_X]/30 mL
INACTIVE INGREDIENTS: water; alcohol

Pleo™ Oku
DROPS 2X

Homeopathic
Antidiarrheal
Medicine

1 fl oz
(30 mL)

Indications

For temporary relief of acute diarrhea.

INGREDIENTS

30 mL Okoubaka aubrevillei 2X in a base of purified water, ethanol (70%).

Tamper Evident

Do not use this product if tamper-evident seal on base of bottle cap is missing or broken or if imprinted security strip on carton is torn.

DOSAGE

Acute

5 drops, every ½ to 1 hour;

Chronic

5 drops, 1-3 times daily.

WARNING

lf symptoms persist more than a few days, contact a licensed practitioner. As with any other drug, if you are pregnant or nursing a baby, seek the advice of a health care professional before using this product.

KEEP OUT OF REACH OF CHILDREN

Keep this and all medications out of the reach of children. In case of accidental overdose, seek professional assistance or contact a Poison Control Center immediately.

STORAGE AND HANDLING

Protect from light and heat.

Made in Germany.

Distributed by:
SANUM USA Corp.
1465 Slater Road
Ferndale, WA 98248

Manufactured By:
Sanum-Kehlbeck
GmbH & Co. KG

Rev.12/2007

PRINCIPAL DISPLAY PANEL - 30 mL Label

Pleo™ Oku DROPS 2X

Homeopathic Antidiarrheal Medicine

Indications: For temporary relief of acute diarrhea.

1 fl oz (30 mL)

DOSAGE: Acute: 5 drops every ½ to 1 hour; Chronic: 5 drops, 1–3 times daily. WARNING:
If symptoms persist more than a few days, contact a licensed practitioner. As with any other
drug, if you are pregnant or nursing a baby, seek the advice of a health care professional
before using this product. Keep this and all medications out of the reach of children. In
case of accidental overdose, seek professional assistance or contact a Poison Control Center
immediately. Protect from light and heat. TAMPER EVIDENT: Do not use this product if
tamper-evident seal on base of bottle cap is missing or broken. INGREDIENTS: 30 mL
contains: Okoubaka aubrevillei 2X in a base of purified water, ethanol (70 %). Rev. 06/2009